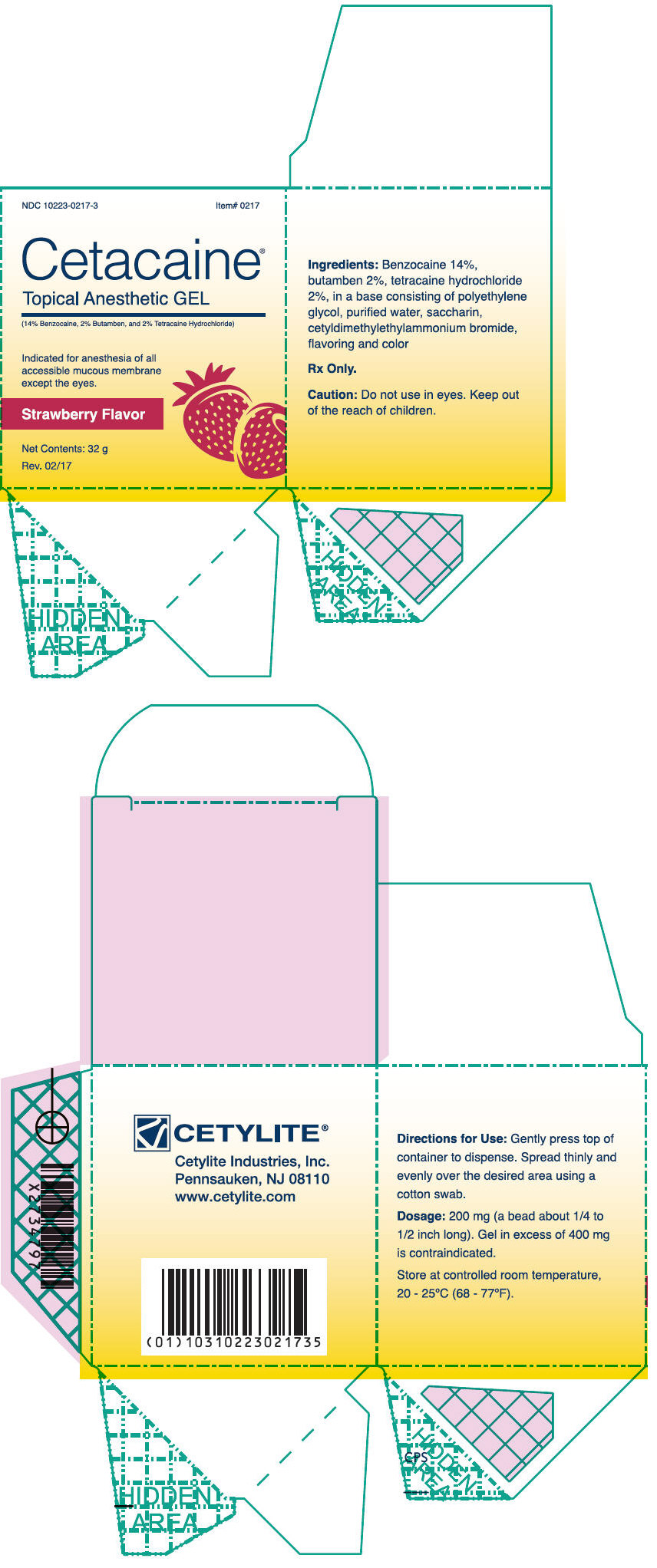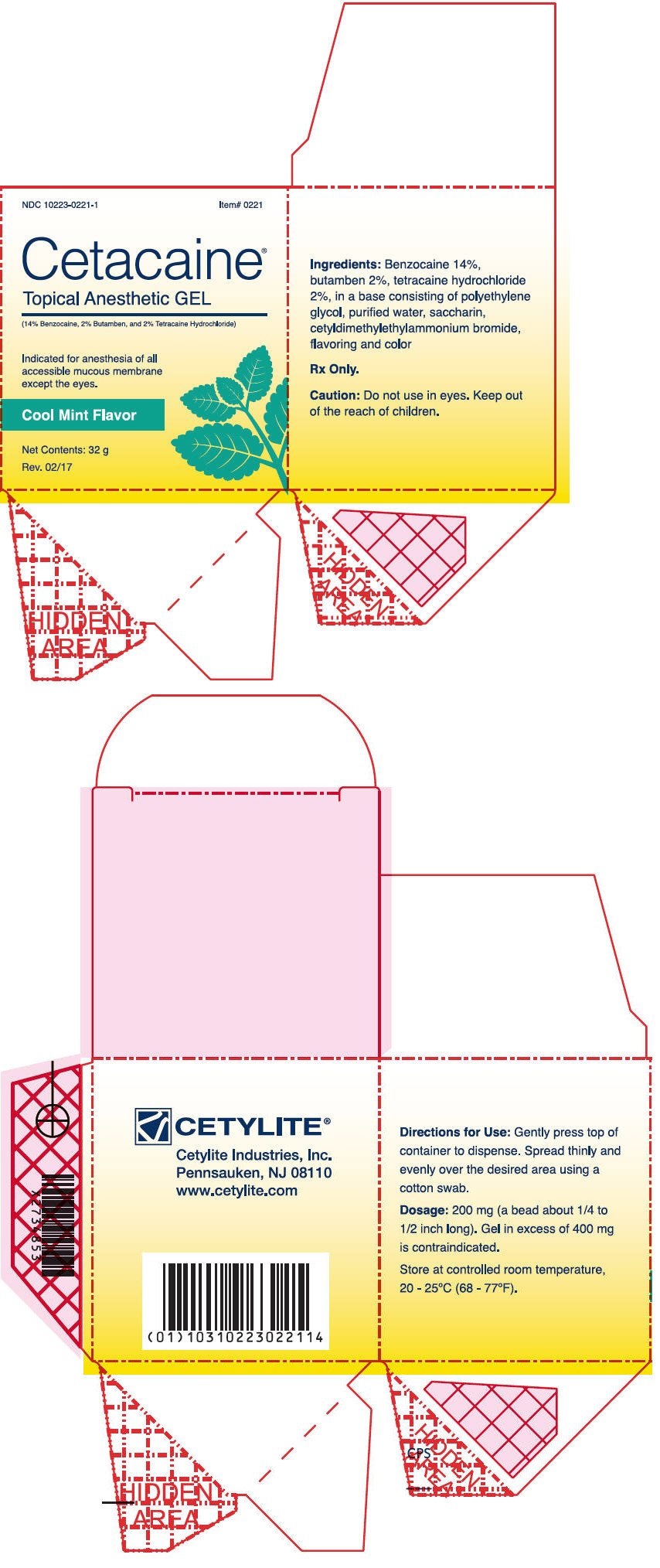 DRUG LABEL: Cetacaine Topical Anesthetic
NDC: 10223-0217 | Form: GEL
Manufacturer: Cetylite Industries, Inc.
Category: prescription | Type: HUMAN PRESCRIPTION DRUG LABEL
Date: 20220117

ACTIVE INGREDIENTS: Benzocaine 0.028 g/0.2 g; Butamben 0.004 g/0.2 g; Tetracaine Hydrochloride 0.004 g/0.2 g
INACTIVE INGREDIENTS: Polyethylene Glycol, Unspecified; Saccharin; Benzalkonium chloride; Mecetronium bromide; Water

Cetacaine®
Topical Anesthetic GEL

Rx Only

DESCRIPTION

Active Ingredients:
Benzocaine | 14.0%
Butamben | 2.0%
Tetracaine Hydrochloride | 2.0%
in a base consisting of polyethylene glycol, purified water, saccharin, cetyldimethylethylammonium bromide, flavoring and color

Action

The onset of Cetacaine Topical Anesthetic Gel produced anesthesia is rapid (approximately 30 seconds) and the duration of anesthesia is typically 30-60 minutes, when used as directed. This effect is due to the rapid onset, but short duration of action of Benzocaine coupled with the slow onset, but extended duration of Tetracaine HCl and bridged by the intermediate action of Butamben.

It is believed that all of these agents act by reversibly blocking nerve conduction. Speed and duration of action is determined by the ability of the agent to be absorbed by the mucous membrane and nerve sheath and then to diffuse out, and ultimately be metabolized (primarily by plasma cholinesterases) to inert metabolites which are excreted in the urine.

Indications

Cetacaine Topical Anesthetic Gel is a topical anesthetic indicated for the production of anesthesia of all accessible mucous membrane except the eyes. Cetacaine Topical Anesthetic Gel is indicated for use to control pain and for use for surgical or endoscopic procedures, or other procedures in the ear, nose, mouth, pharynx, larynx, trachea, bronchi, and esophagus. It may also be used for vaginal or rectal procedures where feasible.

Dosage and Administration

Only a limited quantity of Cetacaine Topical Anesthetic Gel is required for anesthesia.

Dispense 200 mg of gel (a bead approximately 1/4 to 1/2 inches long) by gently depressing the pump. Dispensing a bead of gel in excess of 400 mg is contraindicated. Spread thinly and evenly over the desired area using a cotton swab.

In the unlikely event that a Cetacaine Gel pump jar won't dispense, attempt the following:

1. Using a gloved hand, depress the pump fully using the thumb and middle finger.
2. While depressed, cover the center orifice with the index finger.
3. With the orifice still covered, slowly allow the pump to return to its original starting position.
4. Repeat until Cetacaine Gel is dispensed (usually about 3-4 repeated attempts).

An appropriate pediatric dosage has not been established for Cetacaine Topical Anesthetic Gel.

Dosages should be reduced in the debilitated elderly, acutely ill, and very young patients.

Do not use Cetacaine Gel to treat infants or children younger than 2 years.

Tissue need not be dried prior to application of Cetacaine Topical Anesthetic Gel.

Cetacaine Topical Anesthetic Gel should be applied directly to the site where pain control is required. Anesthesia is produced in approximately 30 seconds with an approximate duration of thirty to sixty minutes. Each 200 mg dose of Cetacaine Topical Anesthetic Gel contains 28 mg of benzocaine, 4 mg of butamben and 4 mg of tetracaine HCl.

WARNINGS AND PRECAUTIONS

Methemoglobinemia

Cases of methemoglobinemia have been reported in association with local anesthetic use. Although all patients are at risk for methemoglobinemia, patients with glucose-6-phosphate dehydrogenase deficiency, congenital or idiopathic methemoglobinemia, cardiac or pulmonary compromise, infants under 6 months of age, and concurrent exposure to oxidizing agents or their metabolites are more susceptible to developing clinical manifestations of the condition. If local anesthetics must be used in these patients, close monitoring for symptoms and signs of methemoglobinemia is recommended.

Signs and symptoms of methemoglobinemia may occur immediately or may be delayed some hours after exposure and are characterized by a cyanotic skin discoloration and abnormal coloration of the blood. Methemoglobin levels may continue to rise; therefore, immediate treatment is required to avert more serious central nervous system and cardiovascular adverse effects, including seizures, coma, arrhythmias, and death. Discontinue Cetacaine and any other oxidizing agents. Depending on the severity of the symptoms, patients may respond to supportive care, i.e., oxygen therapy, hydration.

More severe symptoms may require treatment with methylene blue, exchange transfusion, or hyperbaric oxygen.

DRUG INTERACTIONS

Patients that are administered local anesthetics may be at increased risk of developing methemoglobinemia when concurrently exposed to the following oxidizing agents:

Class | Examples
Nitrates/Nitrites | nitroglycerin, nitroprusside, nitric oxide, nitrous oxide
Local anesthetics | benzocaine, lidocaine, bupivacaine, mepivacaine, tetracaine, prilocaine, procaine, articaine, ropivacaine
Antineoplastic agents | cyclophosphamide, flutamide, rasburicase, ifosfamide, hydroxyurea
Antibiotics | dapsone, sulfonamides, nitrofurantoin, para-aminosalicylic acid
Antimalarials | chloroquine, primaquine
Anticonvulsants | phenytoin, sodium valproate, phenobarbital
Other drugs | acetaminophen, metoclopramide, sulfa drugs (i.e., sulfasalazine), quinine

PATIENT COUNSELING INFORMATION

Inform patients that use of local anesthetics may cause methemoglobinemia, a serious condition that must be treated promptly. Advise patients or caregivers to stop use and seek immediate medical attention if they or someone in their care experience the following signs or symptoms: pale, gray, or blue colored skin (cyanosis); headache; rapid heart rate; shortness of breath; lightheadedness; or fatigue.

Hypersensitivity Reactions

Unpredictable adverse reactions (i.e. hypersensitivity, including anaphylaxis) are extremely rare. Localized allergic reactions may occur after prolonged or repeated use of any aminobenzoate anesthetic. The most common adverse reaction caused by local anesthetics is contact dermatitis characterized by erythema and pruritus that may progress to vesiculation and oozing. This occurs most commonly in patients following prolonged self-medication, which is contraindicated. If rash, urticaria, edema, or other manifestations of allergy develop during use, the drug should be discontinued. To minimize the possibility of a serious allergic reaction, Cetacaine Topical Anesthetic Gel should not be applied for prolonged periods except under continual supervision. Dehydration of the epithelium or an escharotic effect may also result from prolonged contact.

Use in Pregnancy

Safe use of Cetacaine Topical Anesthetic Gel has not been established with respect to possible adverse effects upon fetal development. Therefore, Cetacaine Topical Anesthetic Gel should not be used during early pregnancy, unless in the judgement of a physician, the potential benefits outweigh the unknown hazards. Routine precaution for the use of any topical anesthetic should be observed when Cetacaine Topical Anesthetic Gel is used.

Contraindications

Do not use Cetacaine Gel to treat infants or children younger than 2 years. Cetacaine is not suitable and should never be used for injection. Do not use on the eyes. To avoid excessive systemic absorption, Cetacaine Topical Anesthetic Gel should not be applied to large areas of denuded or inflamed tissue. Cetacaine Topical Anesthetic Gel should not be administered to patients who are hypersensitive to any of its ingredients or to patients known to have cholinesterase deficiencies. Tolerance may vary with status of the patient.

Cetacaine Topical Anesthetic Gel should not be used under dentures or cotton rolls, as retention of the active gel ingredients under a denture or cotton roll could possibly cause an escharotic effect. Routine precaution for the use of any topical anesthetic should be observed when using Cetacaine Topical Anesthetic Gel.

How Supplied

Cetacaine Topical Anesthetic Gel (Strawberry), 32 g jar
NDC 10223-0217-3
Item# 0217

Cetacaine Topical Anesthetic Gel (Mint), 32 g jar
NDC 10223-0221-1
Item# 0221

Made in USA

Cetylite Industries, Inc.
Pennsauken, NJ 08110
www.cetacaine.com

Rev. 10/18

PRINCIPAL DISPLAY PANEL - 32 g Jar Box - Strawberry

NDC 10223-0217-3
Item# 0217

Cetacaine®
Topical Anesthetic GEL

(14% Benzocaine, 2% Butamben, and 2% Tetracaine Hydrochloride)

Indicated for anesthesia of all
accessible mucous membrane
except the eyes.

Strawberry Flavor

Net Contents: 32 g

Rev. 02/17

PRINCIPAL DISPLAY PANEL - 32 g Jar Box - Mint

NDC 10223-0221-1
Item# 0221

Cetacaine®
Topical Anesthetic GEL

(14% Benzocaine, 2% Butamben, and 2% Tetracaine Hydrochloride)

Indicated for anesthesia of all
accessible mucous membrane
except the eyes.

Cool Mint Flavor

Net Contents: 32 g

Rev. 02/17